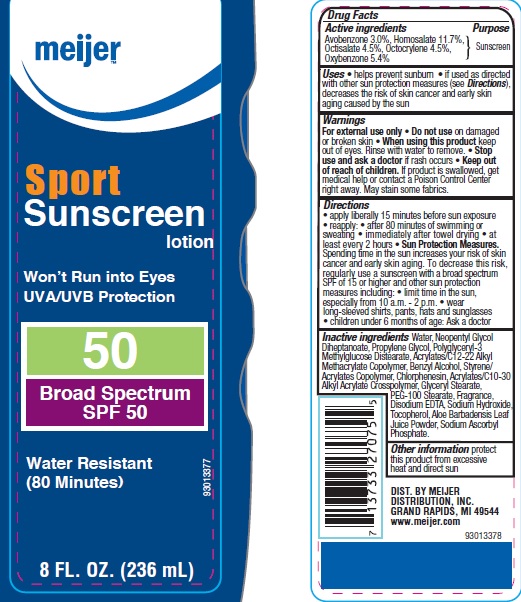 DRUG LABEL: Meijer Sport SPF 50
NDC: 41250-925 | Form: LOTION
Manufacturer: Meijer Distribution, Inc.
Category: otc | Type: HUMAN OTC DRUG LABEL
Date: 20160520

ACTIVE INGREDIENTS: AVOBENZONE 3 g/100 g; HOMOSALATE 11.7 g/100 g; OCTISALATE 4.5 g/100 g; OCTOCRYLENE 4.5 g/100 g; OXYBENZONE 5.4 g/100 g
INACTIVE INGREDIENTS: WATER; NEOPENTYL GLYCOL DIHEPTANOATE; PROPYLENE GLYCOL; BENZYL ALCOHOL; STYRENE; CHLORPHENESIN; GLYCERYL MONOSTEARATE; PEG-100 STEARATE; EDETATE DISODIUM; SODIUM HYDROXIDE; TOCOPHEROL; ALOE VERA LEAF; SODIUM ASCORBYL PHOSPHATE

Drub Facts

Active ingredients

Avobenzone 3.0%, Homosalate 11.7%, Octisalate 4.5%, Octocrylene 4.0%, Oxybenzone 5.4%

Purpose

Sunscreen

Uses

• helps prevent sunburn

• if used as directed with other sun protection measures (see Directions), decreases the risk of skin cancer and early skin aging caused by the sun

Warnings

For external use only

Do not use

on damaged or broken skin

When using this product

keep out of eyes. Rinse with water to remove.

Stop use and ask a doctor

if rash occurs

Keep out of reach of children.

If product is swallowed, get medical help or contact a Poison Control Center right away.

• May stain some fabrics

Directions

• apply liberally 15 minutes before sun exposure

• reapply:

• after 80 minutes of swimming or sweating

• immediately after towel drying

• at least every 2 hours

• Sun Protection Measures: Spending time in the sun increases your risk of skin cancer and early skin aging. To decrease this risk, regularly use a sunscreen with a broad spectrum SPF of 15 or higher and other sun protection measures including:

• limit time in the sun, especially from 10 a.m. to 2 p.m.

• wear long-sleeved shirts, pants, hats, and sunglasses

• children under 6 months: Ask a doctor

Inactive ingredients

Water, Neopentyl Glycol Diheptanoate, Propylene Glycol, Polyglyceryl-3 Methylglucose Distearate, Acrylates/C12-22 Alkyl Methacrylate Copolymer, Benzyl Alcohol, Styrene/Acrylates Copolymer, Chlorphenesin, Acrylates/C10-30 Alkyl Acrylate Crosspolymer, Glyceryl Stearate, PEG-100 Stearate, Fragrance, Disodium EDTA, Sodium Hydroxide, Tocopherol, Aloe Barbadensis Leaf Juice Powder, Sodium Ascorbyl Phosphate.

Other information

protect this product from excessive heat and direct sun

Principal Display Panel

NDC 41250-925-56

meijer

Sport Sunscreen Lotion

Won't Run into Eyes

UVA/UVB Protection

50

Broad Spectrum SPF 50

Water Resistant

(80 Minutes)

8 FL. OZ (236 mL)